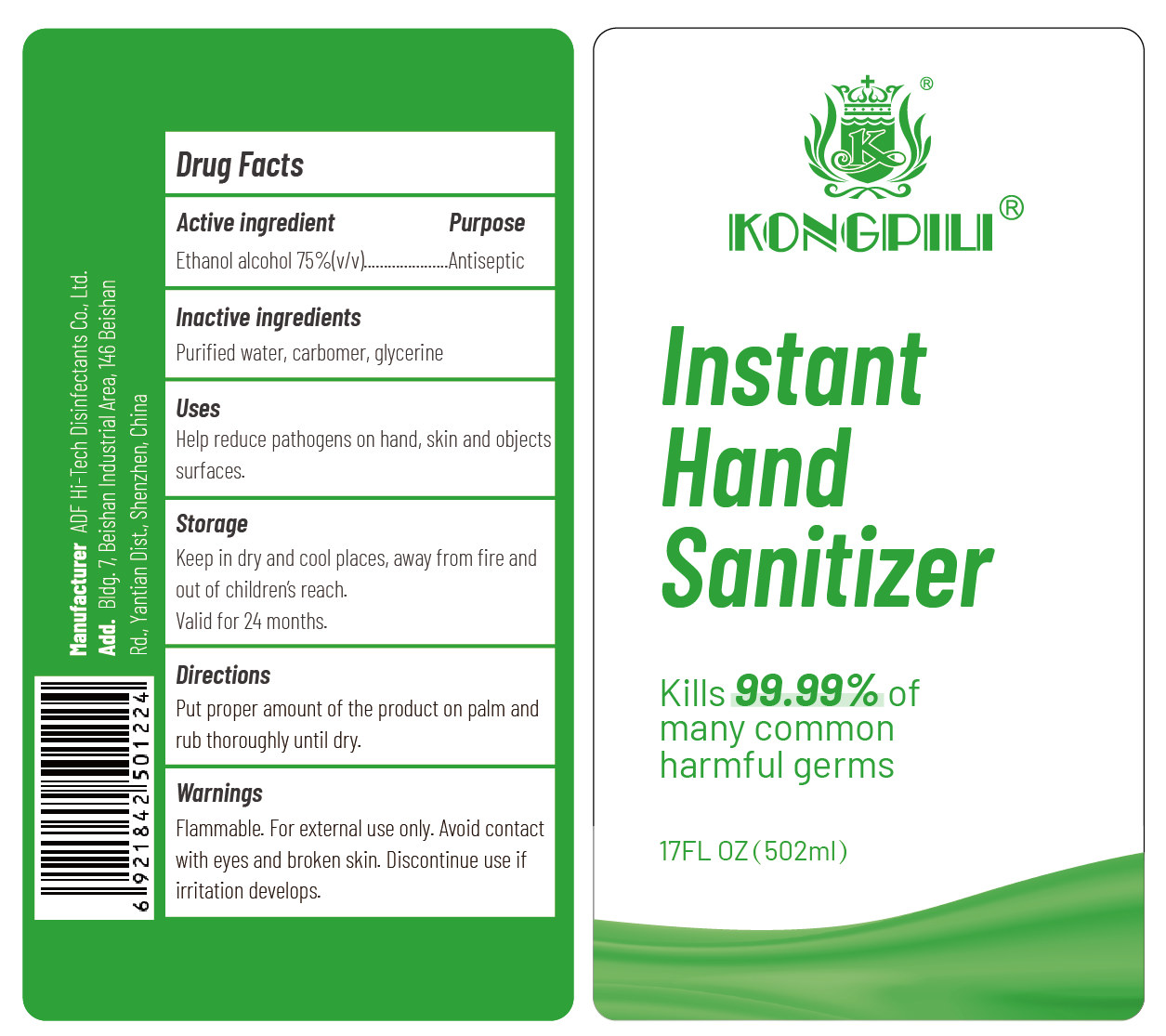 DRUG LABEL: Instant Hand Sanitizer
NDC: 52923-002 | Form: GEL
Manufacturer: ADF HI-TECH DISINFECTANTS CO., LTD.
Category: otc | Type: HUMAN OTC DRUG LABEL
Date: 20200520

ACTIVE INGREDIENTS: ALCOHOL 351.4 mL/502 mL
INACTIVE INGREDIENTS: GLYCERIN; CARBOMER HOMOPOLYMER, UNSPECIFIED TYPE; WATER

DOSAGE AND ADMINISTRATION

Keep in dry and cool places, away from fire.

INACTIVE INGREDIENT

carbomer，glycerine，purified water

INDICATIONS AND USAGE

Put proper amount of the product on palm and rub thoroughly until dry.

ACTIVE INGREDIENT

Ethanol

keep out of reach of children

PURPOSE

Disinfection
Sterilization
No Rinseing

WARNINGS

Flammable. For external use only. Avoid contact with eyes and broken skin. Discontinue use if irritation develops.